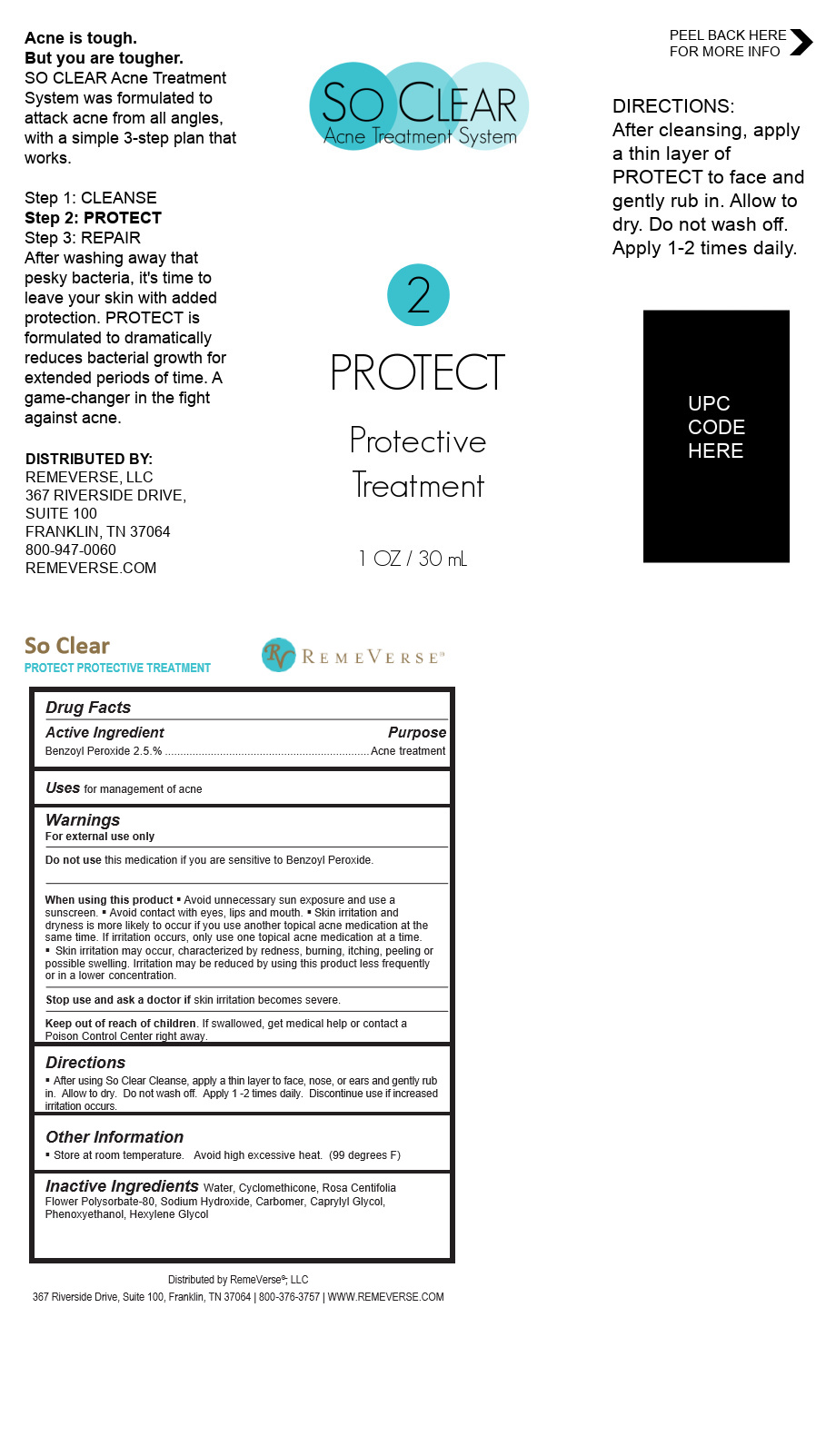 DRUG LABEL: So Clear Protect Protective Treatment
NDC: 70317-147 | Form: CREAM
Manufacturer: RemeVerse
Category: otc | Type: HUMAN OTC DRUG LABEL
Date: 20241216

ACTIVE INGREDIENTS: BENZOYL PEROXIDE 0.8 g/30 mL
INACTIVE INGREDIENTS: POLYSORBATE 80; SODIUM HYDROXIDE; PHENOXYETHANOL; CAPRYLYL GLYCOL; CARBOMER 1342; HEXYLENE GLYCOL; CYCLOMETHICONE; ROSA DAMASCENA FLOWER

So Clear Protect Protective Treatment

So Clear Protect Protective Treatment

Benzoyl Peroxide

So Clear Protect Protective Treatment

Water, Cyclomethicone, Rosa Centifolia Flower Polysorbate-80, Sodium Hydroxide, Carbomer, Caprylyl Glycol, Phenoxyethanol, Hexylene Glycol

Directions

After using So Clear Cleanse, apply a thin layer to face, nose, or ears and gently rub in. Allow to dry. Do not wash off. Apply 1 -2 times daily. Discontinue use if increased irritation occurs.

Uses

for management of acne

Store at room temperature. Avoid high excessive heat. (99 degrees F)

WARNINGS

For external use only

Do not use this medication if you are sensitive to Benzoyl Peroxide.

When using this product § Avoid unnecessary sun exposure and use a sunscreen. § Avoid contact with eyes, lips and mouth. § Skin irritation and dryness is more likely to occur if you use another topical acne medication at the same time. If irritation occurs, only use one topical acne medication at a time.

Skin irritation may occur, characterized by redness, burning, itching, peeling or possible swelling. Irritation may be reduced by using this product less frequently or in a lower concentration.

Stop Use Section

Stop use and ask a doctor if skin irritation becomes severe.

PURPOSE

Acne treatment

Keep out of the reach of Children

. If swallowed, get medical help or contact a Poison Control Center right away.